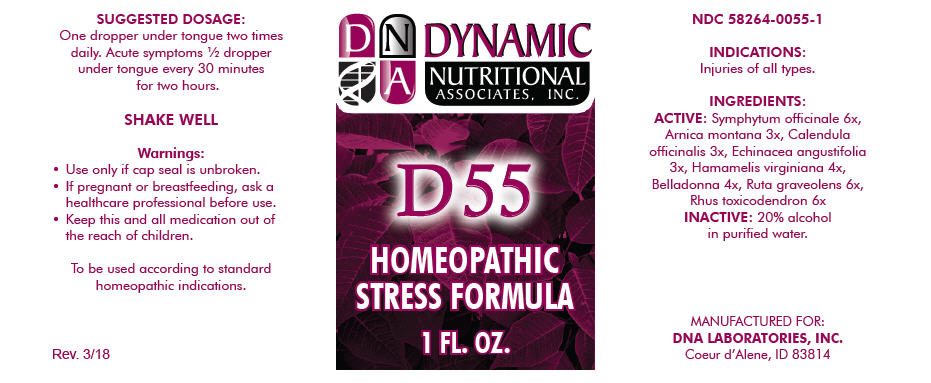 DRUG LABEL: D-55
NDC: 58264-0055 | Form: SOLUTION
Manufacturer: DNA Labs, Inc.
Category: homeopathic | Type: HUMAN OTC DRUG LABEL
Date: 20250113

ACTIVE INGREDIENTS: COMFREY ROOT 6 [hp_X]/1 mL; ARNICA MONTANA 3 [hp_X]/1 mL; CALENDULA OFFICINALIS FLOWERING TOP 3 [hp_X]/1 mL; ECHINACEA ANGUSTIFOLIA 3 [hp_X]/1 mL; HAMAMELIS VIRGINIANA ROOT BARK/STEM BARK 4 [hp_X]/1 mL; ATROPA BELLADONNA 4 [hp_X]/1 mL; RUTA GRAVEOLENS FLOWERING TOP 6 [hp_X]/1 mL; TOXICODENDRON PUBESCENS LEAF 6 [hp_X]/1 mL
INACTIVE INGREDIENTS: ALCOHOL; WATER

D-55

NDC 58264-0055-1

INDICATIONS

PURPOSE

Injuries of all types.

INGREDIENTS

ACTIVE

Symphytum officinale 6x, Arnica montana 3x, Calendula officinalis 3x, Echinacea angustifolia 3x, Hamamelis virginiana 4x, Belladonna 4x, Ruta graveolens 6x, Rhus toxicodendron 6x

INACTIVE

20% alcohol in purified water.

SUGGESTED DOSAGE

One dropper under tongue two times daily. Acute symptoms ½ dropper under tongue every 30 minutes for two hours.

STORAGE AND HANDLING

SHAKE WELL

Warnings

- Use only if cap seal is unbroken.

PREGNANCY OR BREAST FEEDING

- If pregnant or breastfeeding, ask a healthcare professional before use.

KEEP OUT OF REACH OF CHILDREN

- Keep this and all medication out of the reach of children.

To be used according to standard homeopathic indications.

PRINCIPAL DISPLAY PANEL - 1 FL. OZ. Bottle Label

DYNAMIC
NUTRITIONAL
ASSOCIATES, INC.

D 55

HOMEOPATHIC
STRESS FORMULA

1 FL. OZ.